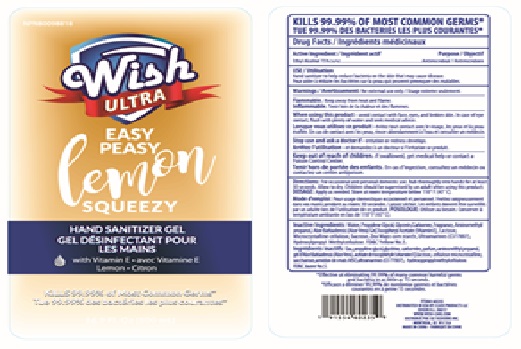 DRUG LABEL: Wish Ultra Hand Sanitizer Easy Peasy Lemon Squeezy
NDC: 71611-053 | Form: GEL
Manufacturer: CLICK PRODUCTS LLC
Category: otc | Type: HUMAN OTC DRUG LABEL
Date: 20200907

ACTIVE INGREDIENTS: ALCOHOL 75 mL/100 mL
INACTIVE INGREDIENTS: MICROCRYSTALLINE CELLULOSE; HYPROMELLOSE, UNSPECIFIED; ULTRAMARINE BLUE; SUCROSE; GLYCERIN; WATER; PROPYLENE GLYCOL; CARBOMER HOMOPOLYMER, UNSPECIFIED TYPE; AMINOMETHYLPROPANOL; ALOE VERA LEAF; .ALPHA.-TOCOPHEROL ACETATE; STARCH, CORN; FD&C YELLOW NO. 5; LACTOSE, UNSPECIFIED FORM

Wish Ultra Hand Sanitizer Easy Peasy Lemon Squeezy

Active Ingredient

Ethyl Alcohol 75% v/v.

Purpose

Antimicrobial

Use

Hand Sanitizer to help reduce bacteria on the skin that may cause disease.

Warnings

For external use only. Flammable. Keep away from heat and flame.

When using this product avoid contat with face, eyes and broken skin. In case of eye contact, flush with plenty of water and seek medical advice.
Stop use and ask a doctor if irritation or redness develops.

Keep out of reach of children. If swallowed, get medical help or contact a Poison Control Center.

Directions

Wet hands thoroughly with product and rub into skin until dry. Children 6 years and younger need adult supervision when using this product.

Other information

Store at temperatures below 110oF (43oC).

Inactive ingredients

Water, Glycerin, Propylene Glycol, Carbomer, Fragrance, Aminomethyl propanol, Aloe Barbadensis (Aloe Vera) Gel, Tocopheryl Acetate (Vitamin E), Lactose, Zea Mays corn starch, Sucrose, Microcrystalline cellulose, Hydroxypropyl Methylcellulose, Ultramarines(I77007) , FD&C Yellow No.5